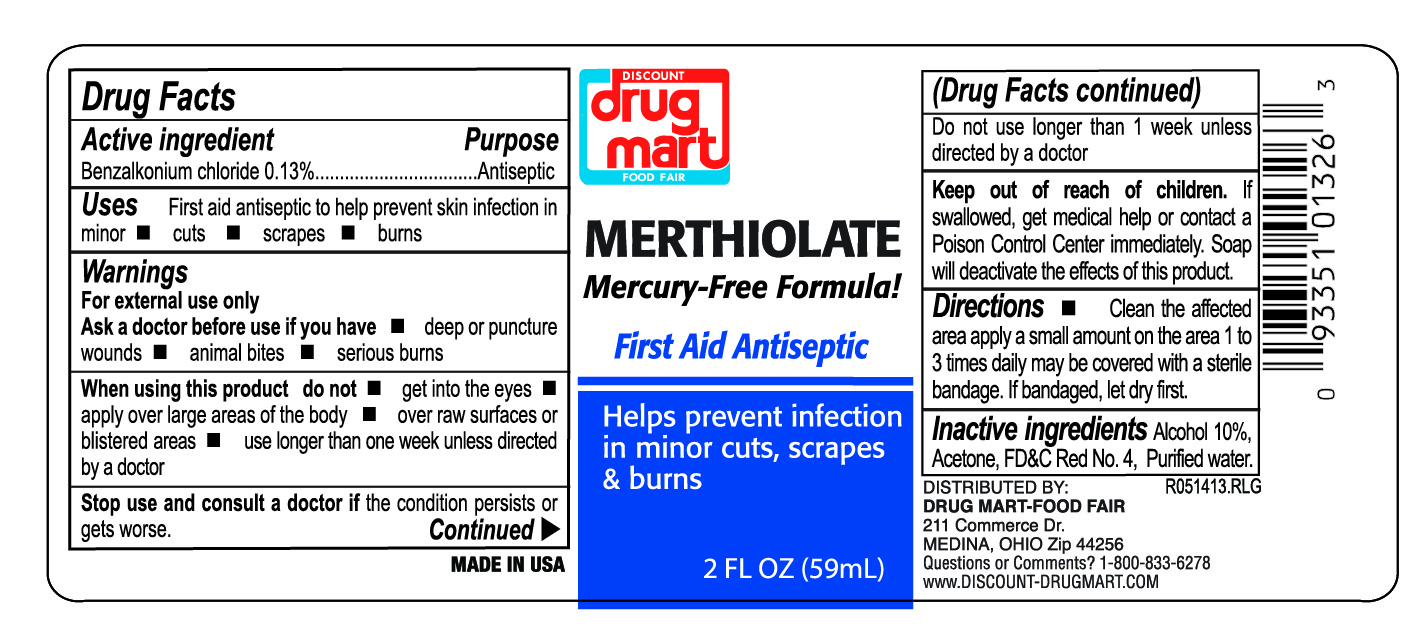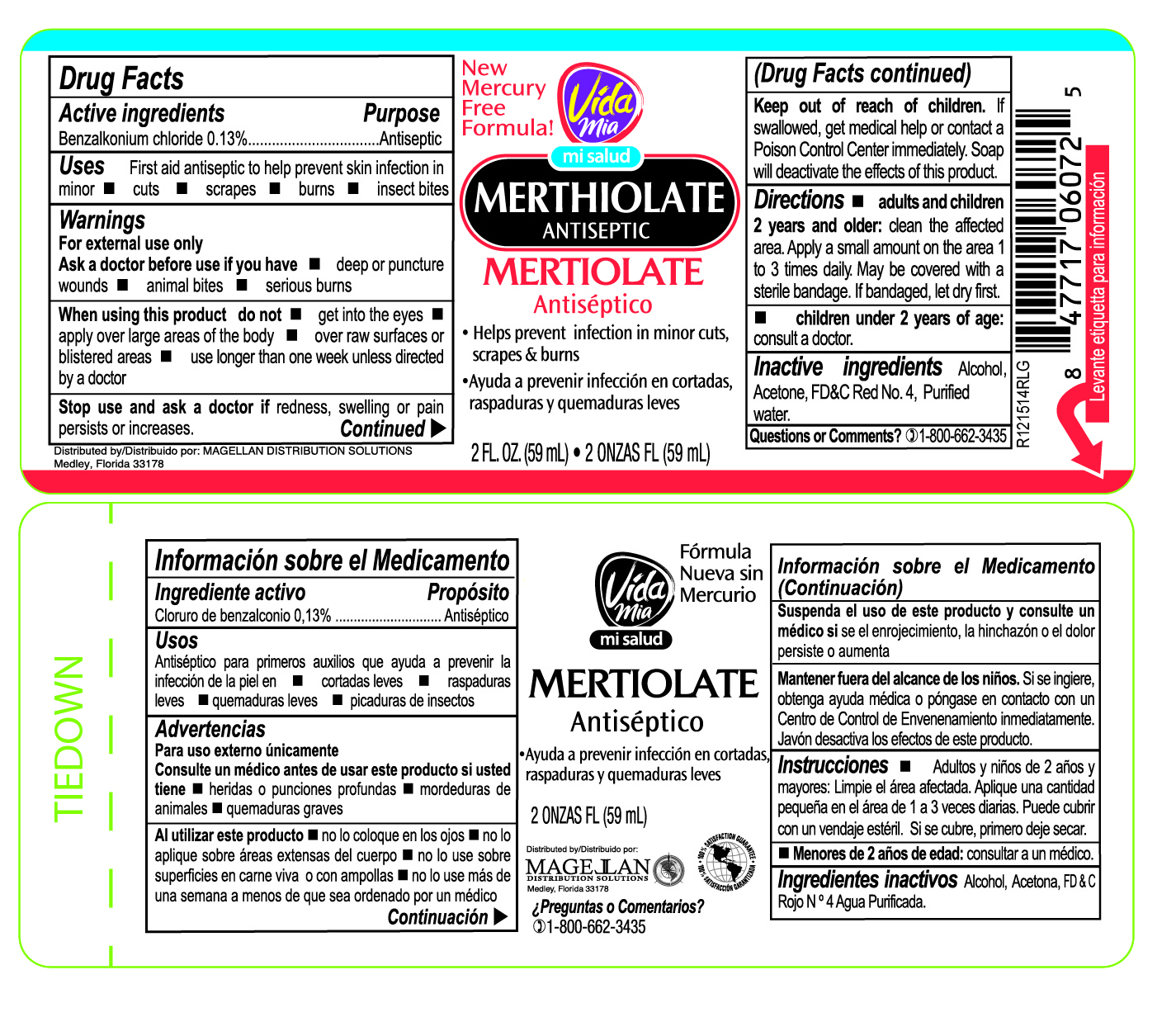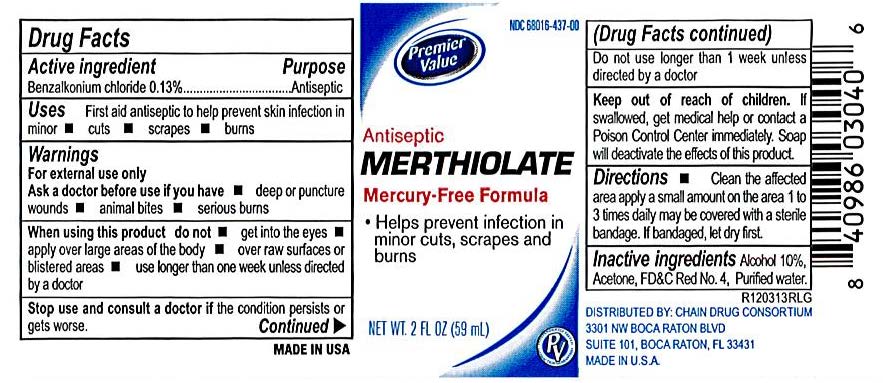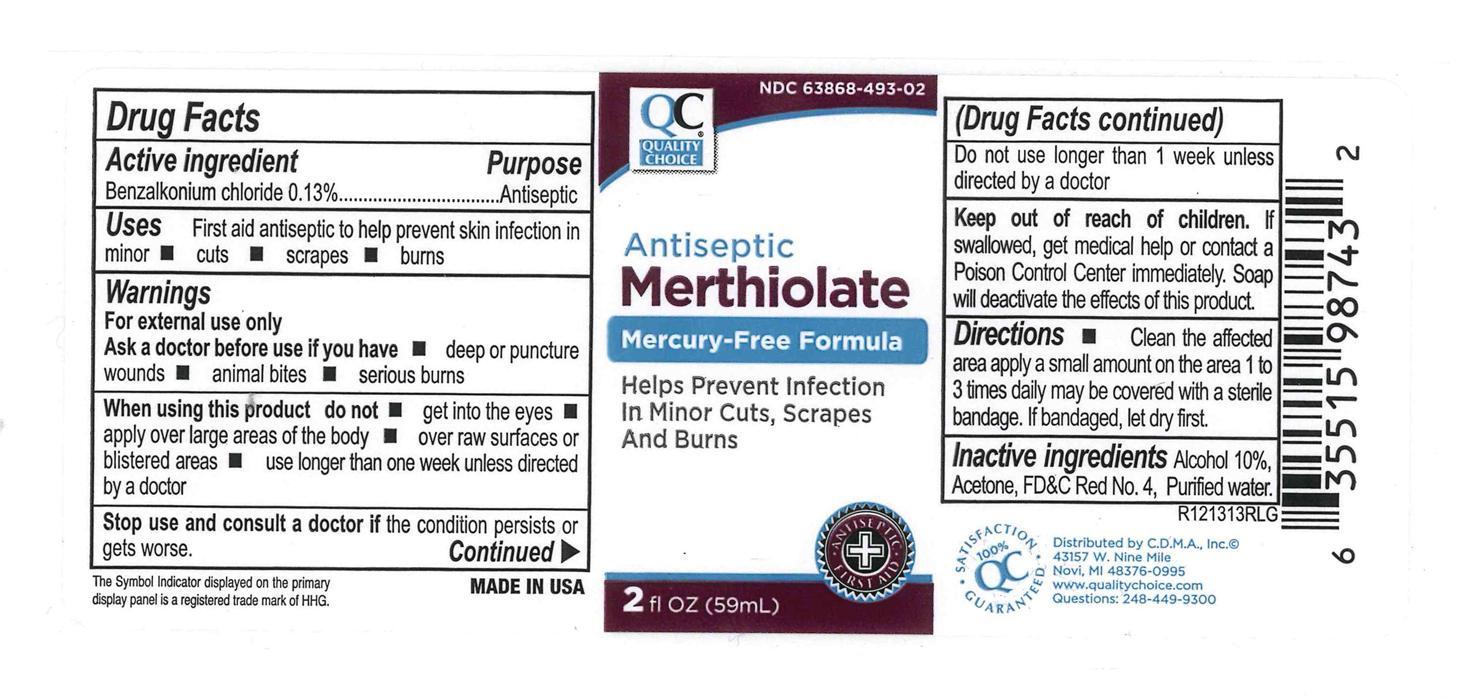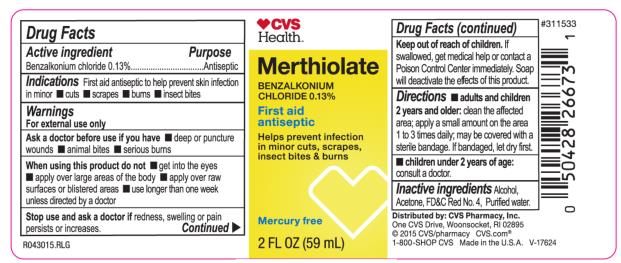 DRUG LABEL: Merthiolate
NDC: 82645-912 | Form: LIQUID
Manufacturer: Pharma Nobis, LLC
Category: otc | Type: HUMAN OTC DRUG LABEL
Date: 20231222

ACTIVE INGREDIENTS: BENZALKONIUM CHLORIDE 1.3 mg/1 mL
INACTIVE INGREDIENTS: WATER; ALCOHOL; ACETONE

Private Label Merthiolate

Drug Facts

Active Ingredient

Benzalkonium chloride 0.13%

Purpose

Antiseptic

Uses

first aid to help prevent skin infection in minor cuts, scrapes, burns and insect bites.

Warnings

For external use only

Ask a doctor before use if you have

deep or puncture wounds, animal bites, serious burns.

When using this product

do not get into eyes. If contact occurs, rinse eyes throughly with water. do not apply over large areas of the body. do not use over raw surfaces or blistered areas. do not use longer than 1 week unless directed by a doctor.

Stop use and aska doctor if

condition persists or gets worse. symptoms clear up and occur again within a few days.

Keep out of reach of children

If swallowed, get medical help or contact a Poison Control Center immediately.

Directions

adults and children 2 years and older. clean the affected area. apply a small amount on the area 1 to 3 times daily. may be covered with a sterile bandage. if bandaged, let it dry first. children under 2 years of age, do not use, consult a doctor.

Inactive ingredients

Alcohol 10%, Acetone, FD&C Red No 4, purified water